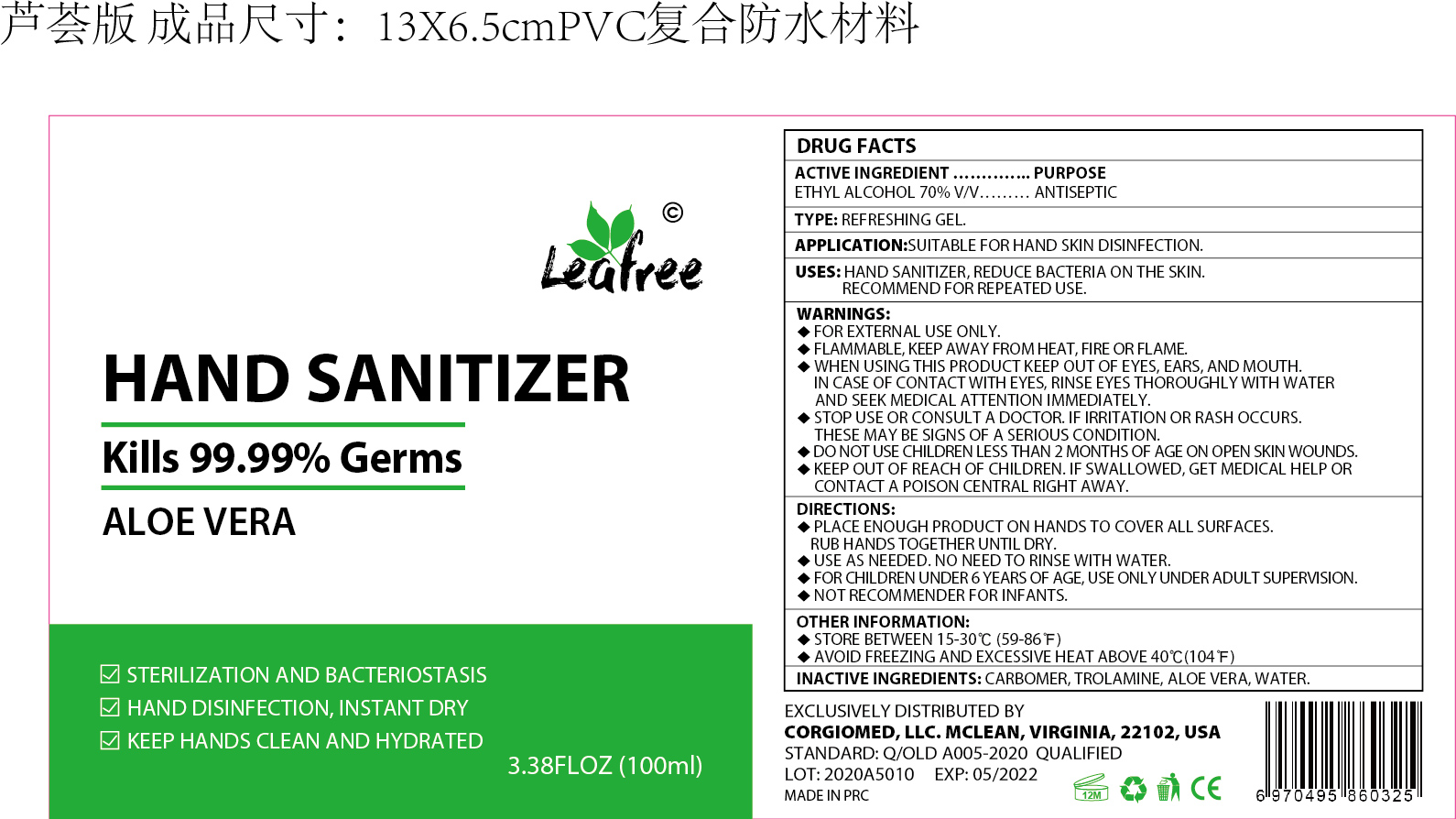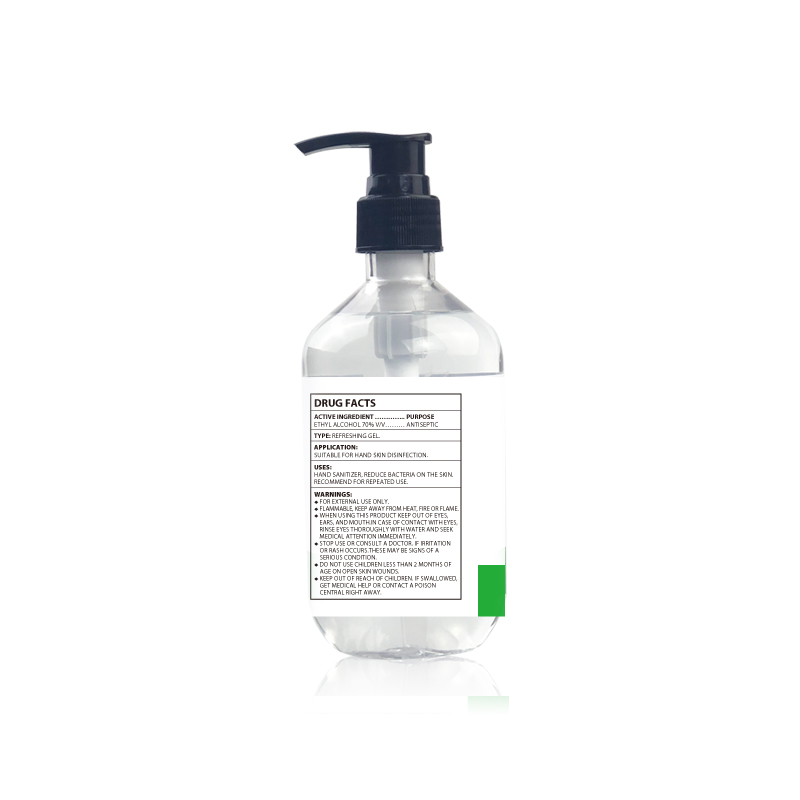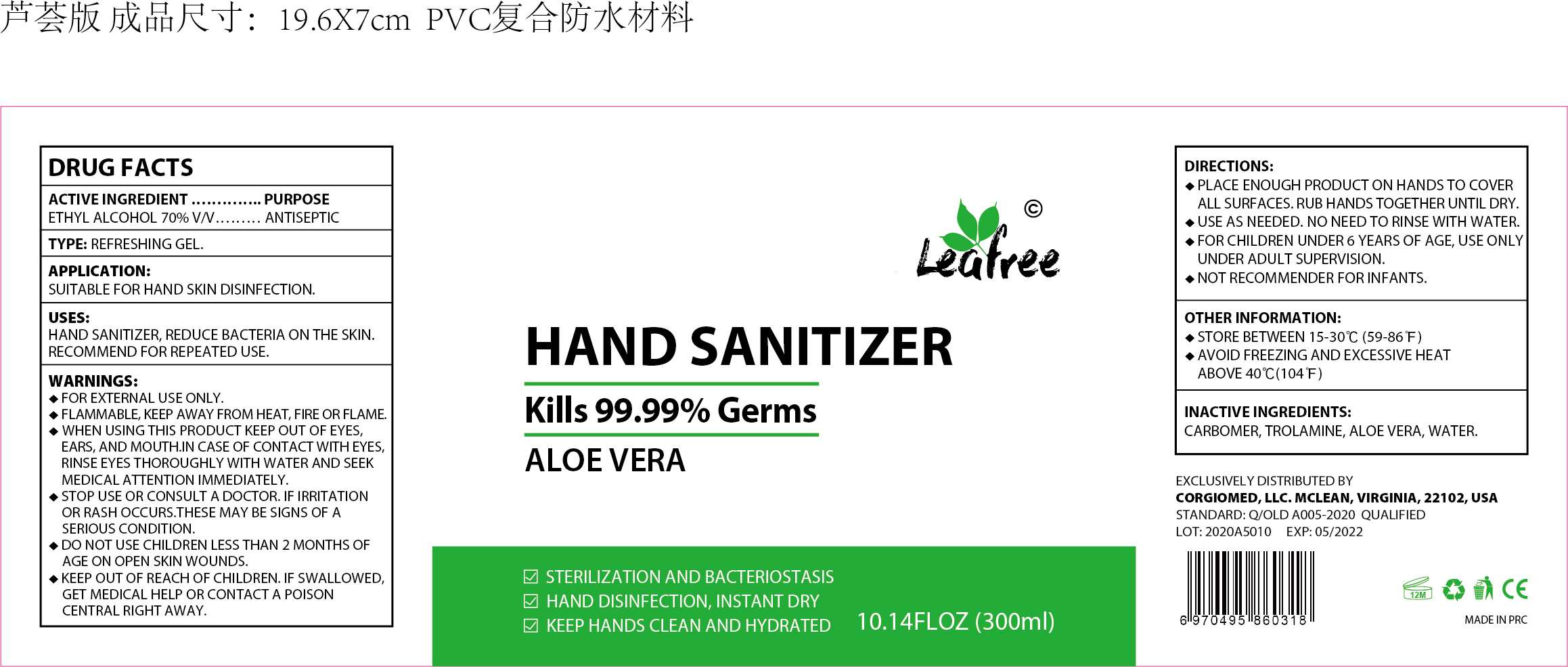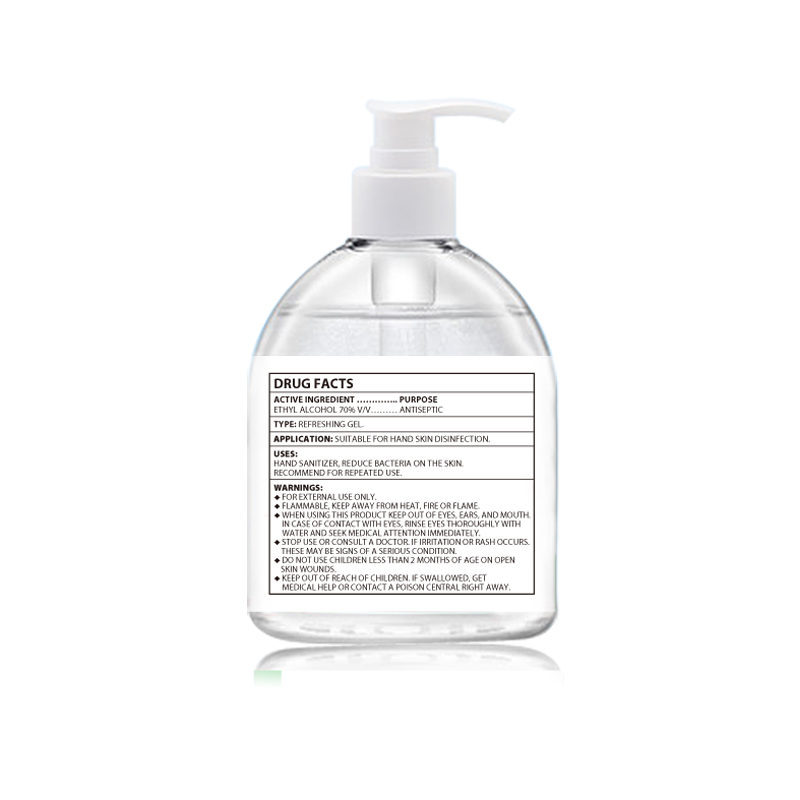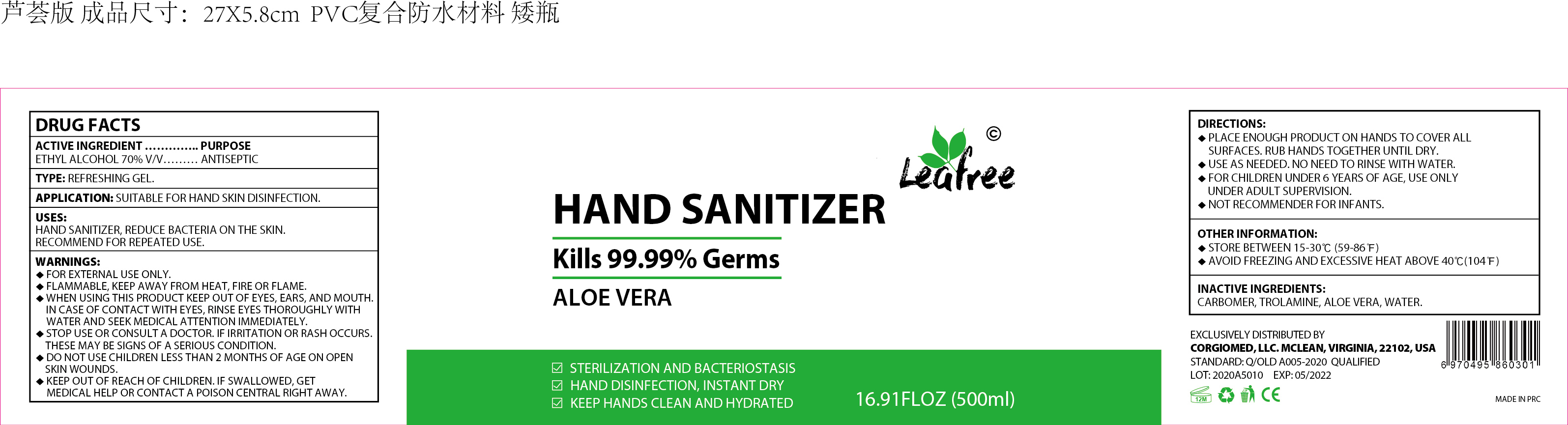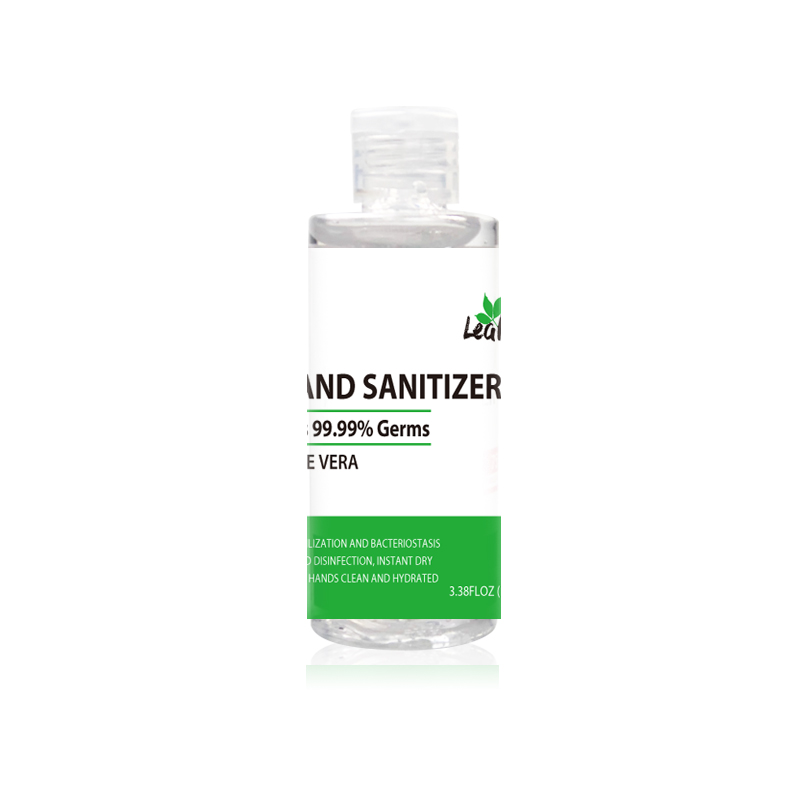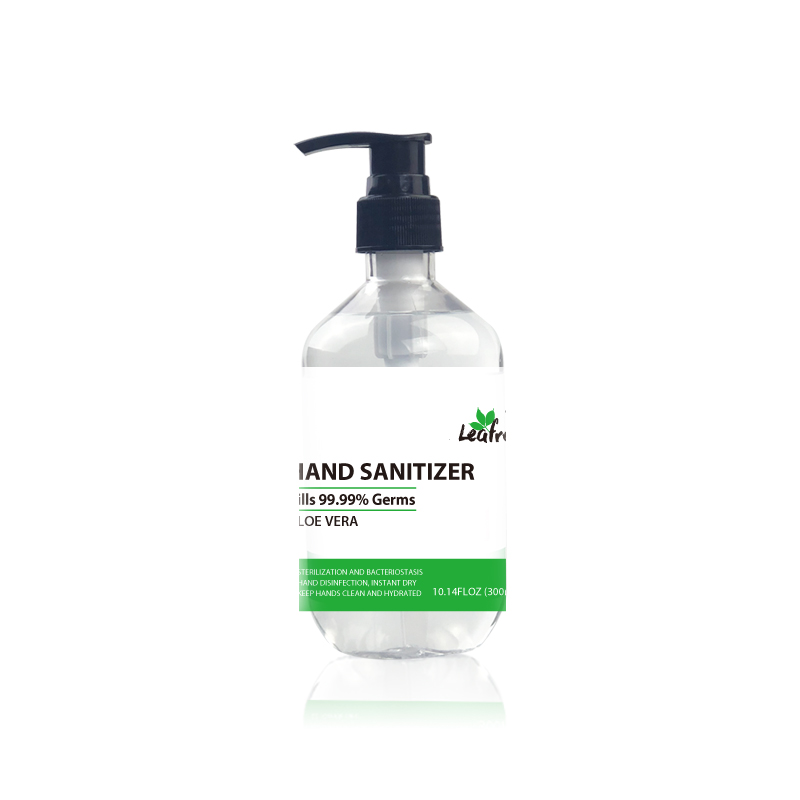 DRUG LABEL: Leafree Hand Sanitizer with ALOE VERA16.91oz
NDC: 76573-822 | Form: GEL
Manufacturer: Corgiomed,LLC
Category: otc | Type: HUMAN OTC DRUG LABEL
Date: 20200426

ACTIVE INGREDIENTS: ALCOHOL 70 mL/100 mL
INACTIVE INGREDIENTS: ALOE VERA LEAF 0.2 mL/100 mL; CARBOMER 980 0.24 mL/100 mL; TROLAMINE 0.2 mL/100 mL; WATER 29.36 mL/100 mL

This is a hand sanitizer manufactured according to the Temporary Policy for Preparation of Certain Alcohol-Based Hand Sanitizer Products During the Public Health Emergency (CoViD-19); Guidance for Industry.

The hand sanitizer is manufactured using only the following United States Pharmacopoeia (USP) grade ingredients in the preparation of the product (percentage in final product formulation) consistent with World Health Organization (WHO) recommendations:

1. Alcohol (ethanol) (USP or Food Chemical Codex (FCC) grade) (70%, volume/volume (v/v)) in an aqueous solution denatured according to Alcohol and Tobacco Tax and Trade Bureau regulations in 27 CFR part 20.
2. Carbomer
3. Trolamine
4. Aloe Vera
5. Sterile distilled water or boiled cold water.

The firm does not add other active or inactive ingredients. Different or additional ingredients may impact the quality and potency of the product.

Active Ingredient(s)

Ethyl Alcohol 70% v/v. Purpose: Antiseptic

Purpose

Antiseptic, Hand Sanitizer

Use

Uses:
Hand Sanitizer, reduce bacteria on the skin
Recommend for repeated use

Warnings

For external use only
Flammable, keep away from heat, fire or flame

Warnings:

Do not use Children less than 2 months of age on open skin wounds
Keep out of reach of children. If swallowed, get medical help or contact a poison Central right away

When using this product keep out of eyes, ears, and mouth. In case of contact with eyes, rinse eyes thoroughly with water.
Stop use and ask a doctor if irritation or rash occurs. These may be signs of a serious condition.
Keep out of reach of children. If swallowed, get medical help or contact a Poison Control Center right away.

Stop use and ask a doctor if irritation or rash occurs. These may be signs of a serious condition.

Keep out of reach of children. If swallowed, get medical help or contact a Poison Control Center right away.

Directions

Place enough product on hands to cover all surfaces. Rub hands together until dry.
Use as needed. No need to rinse with water
For children under 6 years of age, use only under adult supervision.
Not recommender for infants

Other information

- Store between 15-30C (59-86F)
- Avoid freezing and excessive heat above 40C (104F)

Inactive ingredients

CARBOMER, TROLAMINE, ALOE VERA, WATER.

Package Label - Principal Display Panel

100 mL NDC:76573-820-10

300 ml NDC: 76573-821-11

500 ml NDC: 76573-822-12